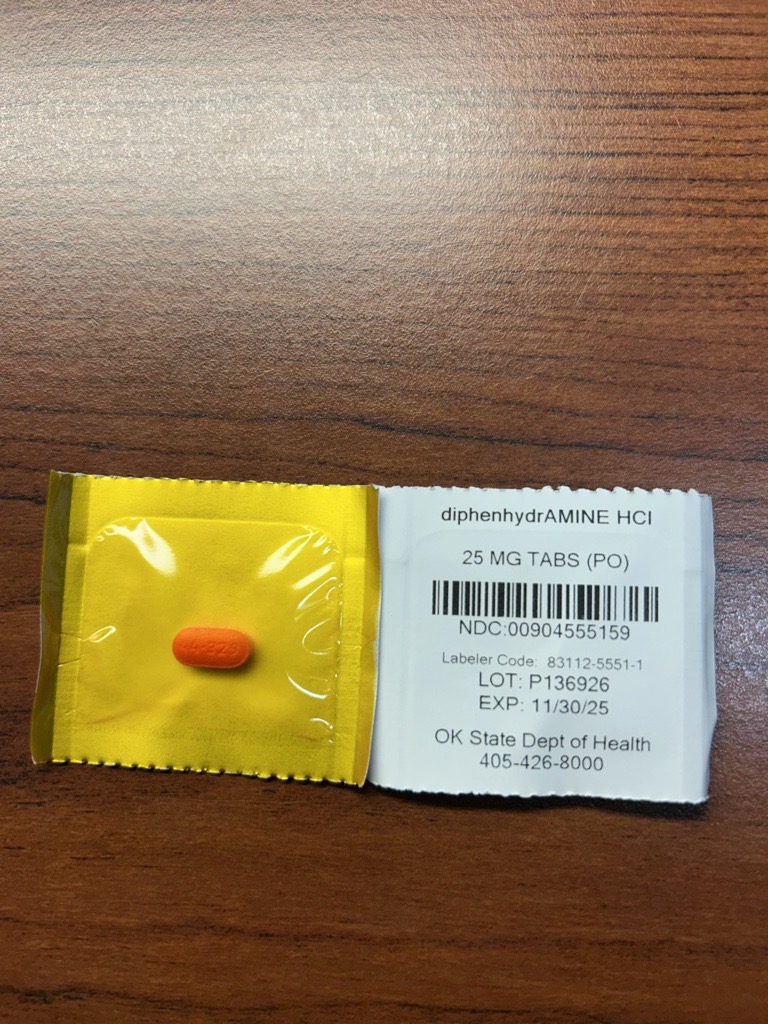 DRUG LABEL: Banophen
NDC: 83112-555 | Form: TABLET, FILM COATED
Manufacturer: Health Department, Oklahoma State
Category: prescription | Type: HUMAN PRESCRIPTION DRUG LABEL
Date: 20250129

ACTIVE INGREDIENTS: DIPHENHYDRAMINE HYDROCHLORIDE 25 mg/1 1

Diphenhydramine 25mg (Emergency Kits)

WHEN USING

marked drowsiness may occur
avoid alcoholic beverages
alcohol, sedatives, and tranquilizers may increase drowsiness
use caution when driving a motor vehicle or operating machinery
excitability may occur, especially in children